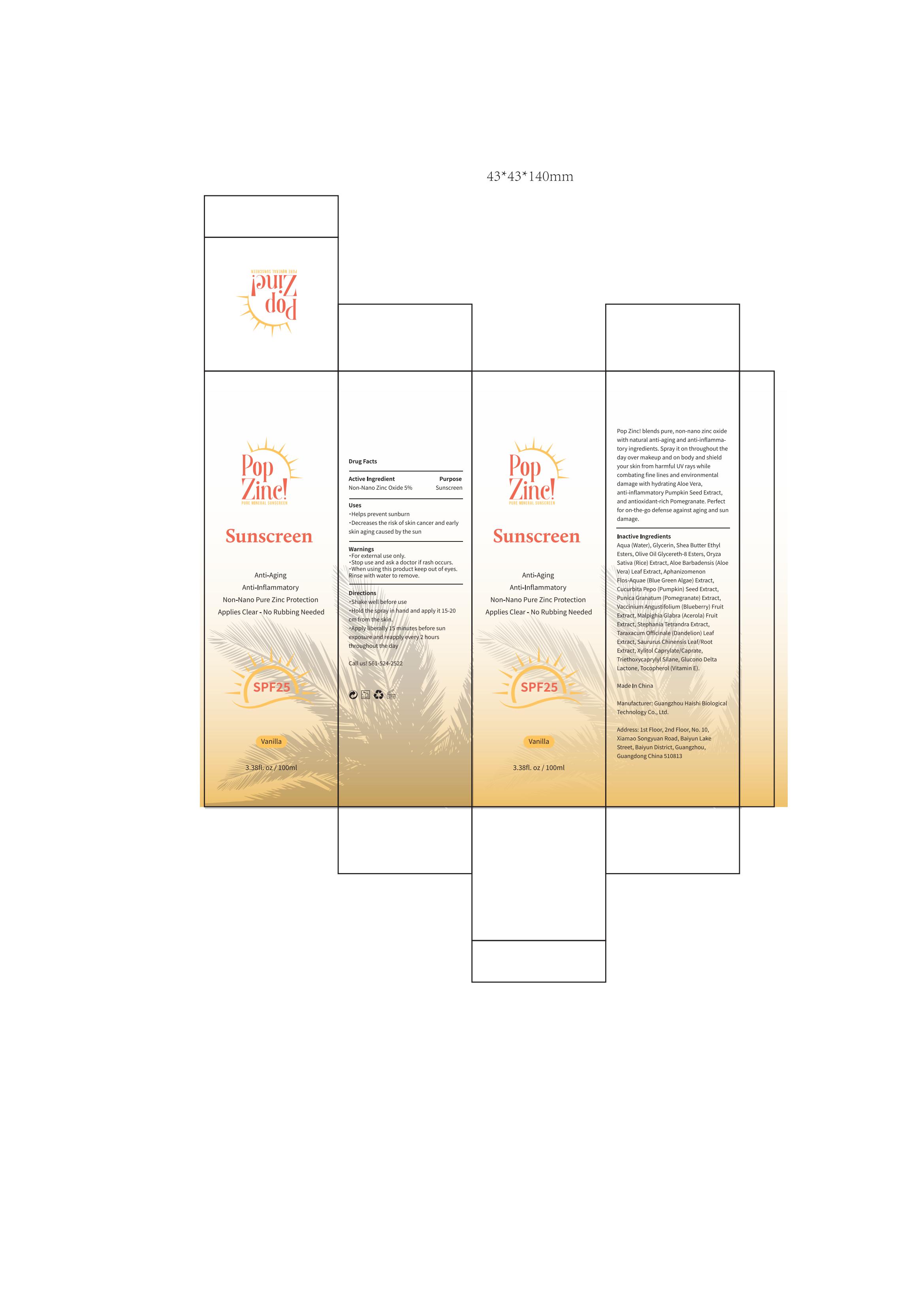 DRUG LABEL: Pop Zinc Sunscreen
NDC: 60771-0009 | Form: SPRAY
Manufacturer: Guangzhou Haishi Biological Technology Co., Ltd
Category: otc | Type: HUMAN OTC DRUG LABEL
Date: 20250107

ACTIVE INGREDIENTS: ZINC OXIDE 5 g/100 mL
INACTIVE INGREDIENTS: TRIETHOXYCAPRYLYLSILANE; TOCOPHEROL; MALPIGHIA GLABRA (ACEROLA) FRUIT; OLIVE OIL GLYCERETH-8 ESTERS; SHEA BUTTER ETHYL ESTERS; APHANIZOMENON FLOSAQUAE; GLYCERIN

Pop Zinc Sunscreen

Active ingredients

Non-Nano Zinc Oxide 5%

Purpose

Sunscreen

Warnings

For external use only.

Stop use and ask a doctor if

rash occurs.

Do not use

on damaged or broken skin.

When using this product

keep out of eyes. Rinse with water to remove.

Keep out of reach of children.

If swallowed, get medical help or contact a Poison Control Center right away.

Dosage

Squeeze out an appropriate amount of product and spread evenly on skin.

Inactive ingredients

AQUA (WATER) 67.6%
GLYCERIN 5%
SHEA BUTTER ETHYL ESTERS 5%
OLIVE OIL GLYCERETH-8 ESTERS 6%
ORYZA SATIVA (RICE) EXTRACT 0.8%
ALOE BARBADENSIS (ALOE VERA) LEAF EXTRACT 0.8%
APHANIZOMENON FLOSAQUAE (BLUE GREEN ALGAE) EXTRACT 0.8%
CUCURBITA PEPO (PUMPKIN) SEED EXTRACT 1%
PUNICA GRANATUM (POMEGRANATE) EXTRACT 1%
VACCINIUM ANGUSTIFOLIUM (BLUEBERRY) FRUIT EXTRACT 0.5%
MALPIGHIA GLABRA (ACEROLA) FRUIT EXTRACT 0.5%
STEPHANIA TETRANDRA EXTRACT 0.5%
TARAXACUM OFFICINALE (DANDELION) LEAF EXTRACT 0.5%
SAURURUS CHINENSIS LEAF/ROOT EXTRACT 0.5%
XYLITOL CAPRYLATE/CAPRATE 1%
TRIETHOXYCAPRYLYLSILANE 1.5%
GLUCONO DELTA LACTONE 1%
TOCOPHEROL 1%

Uses

Shake well before use.
Hold the spray in hand and apply it 15-20cm from the skin.
Apply liberally 15 minutes before sun
exposure and reapply every 2 hoursthroughout the day